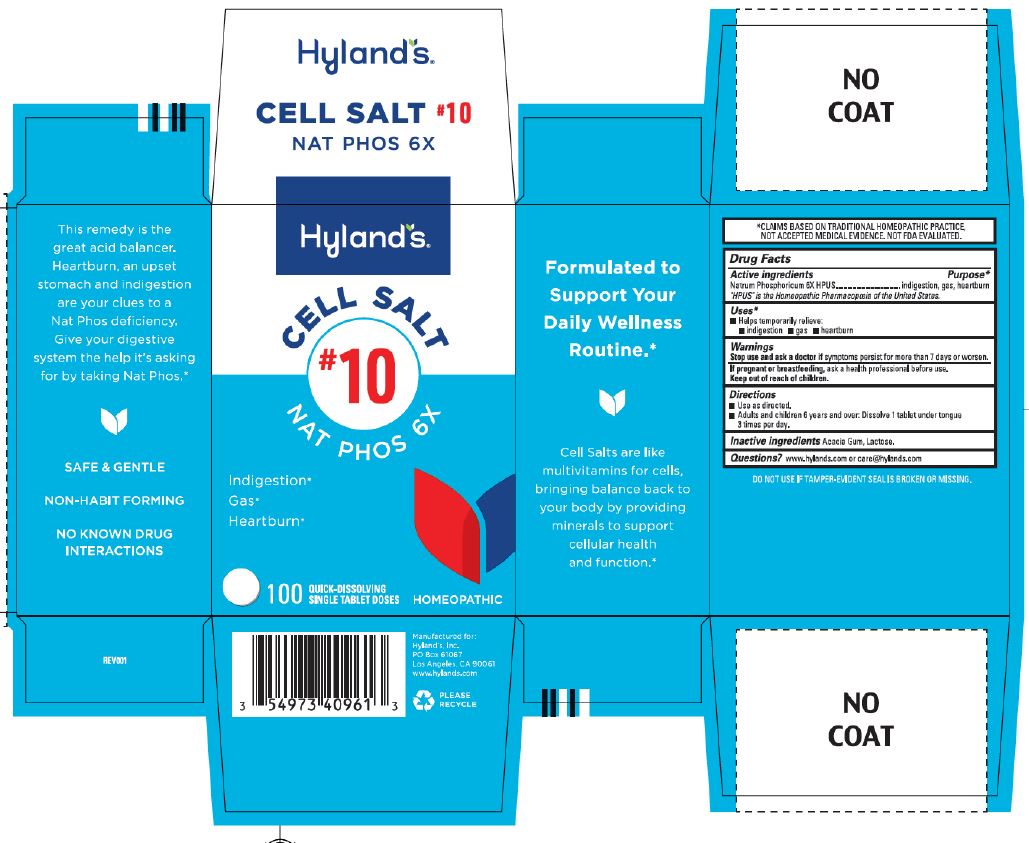 DRUG LABEL: Nat Phos 6X
NDC: 54973-4096 | Form: TABLET, SOLUBLE
Manufacturer: Hyland's Inc.
Category: homeopathic | Type: HUMAN OTC DRUG LABEL
Date: 20250709

ACTIVE INGREDIENTS: SODIUM PHOSPHATE, DIBASIC, HEPTAHYDRATE 6 [hp_X]/1 1
INACTIVE INGREDIENTS: LACTOSE MONOHYDRATE; ACACIA

Cell Salt #10 Nat Phos 6X

Purpose

Indigestion

Gas

Heartburn

Drug Facts

Active ingredients | Purpose
Natrum Phosphoricum 6X HPUS | indigestion, gas, heartburn

"HPUS" is the Homeopathic Pharmacopoeia of the United States.

Uses

■ Temporarily relieves:
■ indigestion ■ gas ■ heartburn

Warnings

Stop use and ask a doctor if

Symptoms persist for more than 7 days or worsen.

If pregnant or breastfeeding

Ask a health professional before use.

Directions

■ Use as directed.
■ Adults and children 6 years and over: Dissolve 1 tablet under tongue 3 times per day.

Inactive ingredients

Acacia Gum, Lactose.

Questions?

www.hylands.com or care@hylands.com

PRINCIPAL DISPLAY PANEL

Hyland's

CELL SALT

#10

NAT PHOS 6X

Indigestion*

Gas*

Heartburn*

100

QUICK-DISSOLVING

SINGLE TABLET DOSES

HOMEOPATHIC